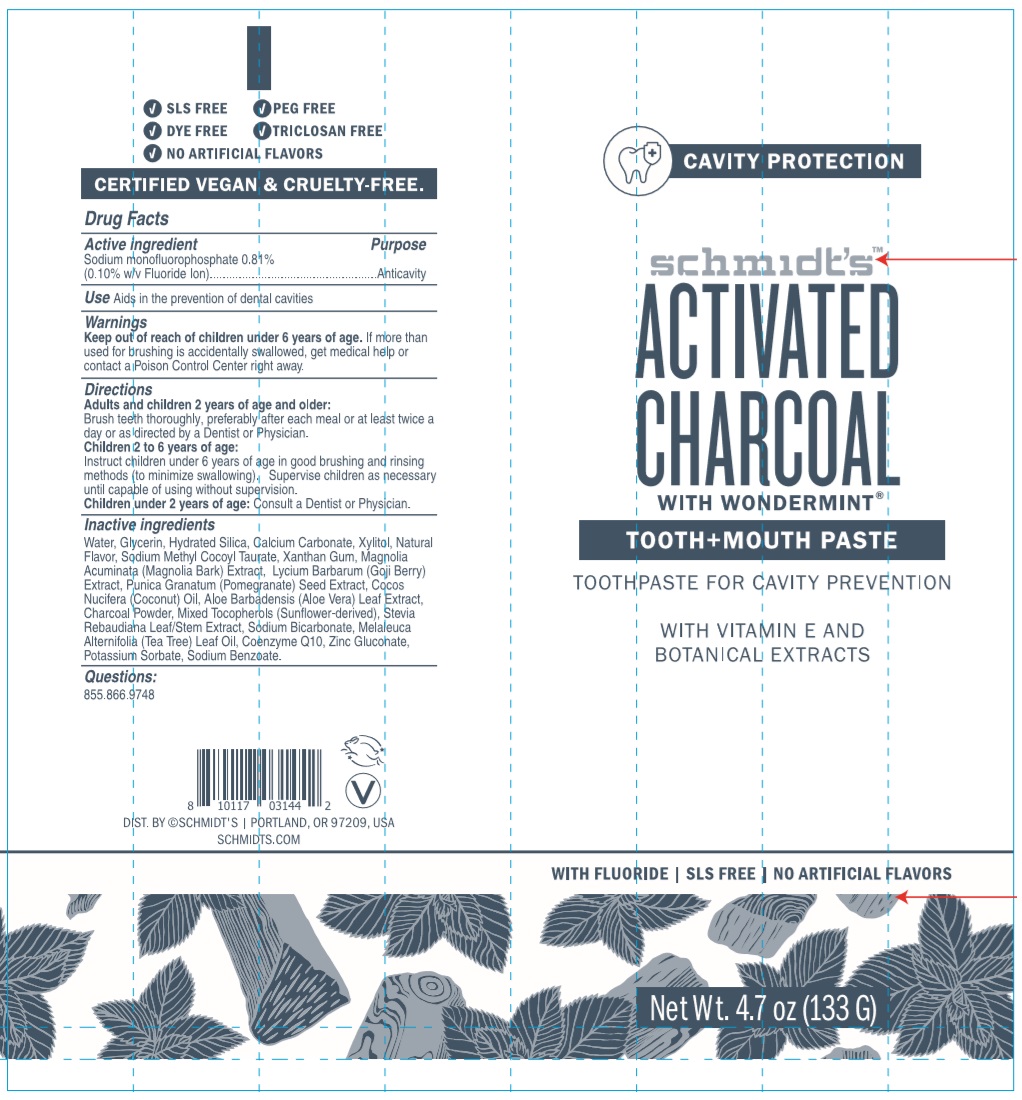 DRUG LABEL: Schmidts
NDC: 72916-112 | Form: PASTE, DENTIFRICE
Manufacturer: Schmidt's Naturals
Category: otc | Type: HUMAN OTC DRUG LABEL
Date: 20190614

ACTIVE INGREDIENTS: SODIUM MONOFLUOROPHOSPHATE 1.079 g/133 g
INACTIVE INGREDIENTS: WATER; GLYCERIN; HYDRATED SILICA; CALCIUM CARBONATE; XYLITOL; SODIUM METHYL COCOYL TAURATE; XANTHAN GUM; MAGNOLIA ACUMINATA BARK; LYCIUM BARBARUM FRUIT; POMEGRANATE SEED; COCONUT OIL; ALOE VERA LEAF; ACTIVATED CHARCOAL; TOCOPHEROL; STEVIA REBAUDIUNA LEAF; SODIUM BICARBONATE; TEA TREE OIL; UBIDECARENONE; ZINC GLUCONATE; POTASSIUM SORBATE; SODIUM BENZOATE

Schmidt's™-ACTIVATED CHARCOAL WITH WONDERMINT® TOOTH+MOUTH PASTE

Active ingredient

Sodium monofluorophosphate 0.81%
(0.10% w/v Fluoride Ion)

Purpose

Anticavity

Use

Aids in the prevention of dental cavities

Warnings

Keep out of reach of children under 6 years of age. If more than used for brushing is accidentally swallowed, get medical help or contact a Poison Control Center right away.

Directions

Adults and children 2 years of age and older:
Brush teeth thoroughly, preferably after each meal or at least twice a day or as directed by a Dentist or Physician.
Children 2 to 6 years of age:
Instruct children under 6 years of age in good brushing and rinsing methods (to minimize swallowing). Supervise children as necessary until capable of using without supervision.
Children under 2 years of age: Consult a Dentist or Physician.

Inactive ingredients

Water, Glycerin, Hydrated Silica, Calcium Carbonate, Xylitol, Natural Flavor, Sodium Methyl Cocoyl Taurate, Xanthan Gum, Magnolia Acuminata (Magnolia Bark) Extract, Lycium Barbarum (Goji Berry) Extract, Punica Granatum (Pomegranate) Seed Extract, Cocos Nucifera (Coconut) Oil, Aloe Barbadensis (Aloe Vera) Leaf Extract, Charcoal Powder, Mixed Tocopherols (Sunflower-derived), Stevia Rebaudiana Leaf/Stem Extract, Sodium Bicarbonate, Melaleuca Alternifolia (Tea Tree) Leaf Oil, Coenzyme Q10, Zinc Gluconate, Potassium Sorbate, Sodium Benzoate.

Questions:

855.866.9748

CAVITY PROTECTION

TOOTHPASTE FOR CAVITY PREVENTION

WITH VITAMIN E AND BOTANICAL EXTRACTS

WITH FLUORIDE | SLS FREE | NO ARTIFICIAL FLAVORS

√ PEG FREE √ DYE FREE √ TRICLOSAN FREE

CERTIFIED VEGAN & CRUELTY-FREE.

DIST. BY ©SCHMIDT'S | PORTLAND, OR 97209, USA
SCHMIDTS.COM